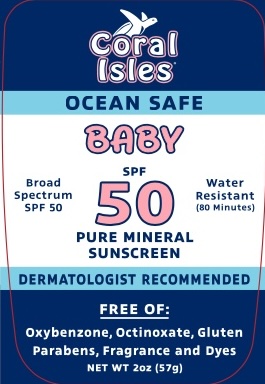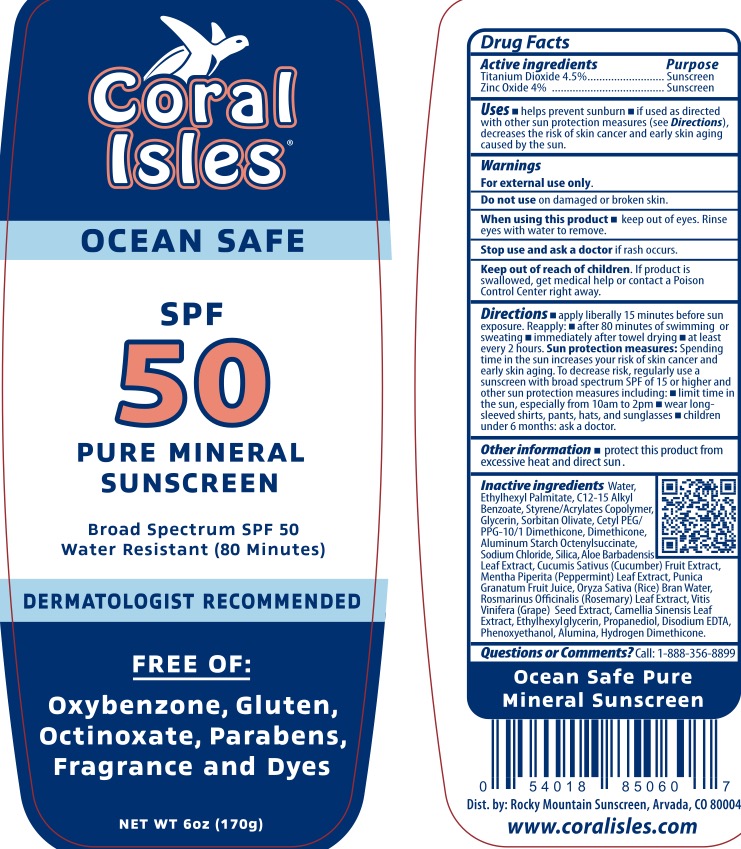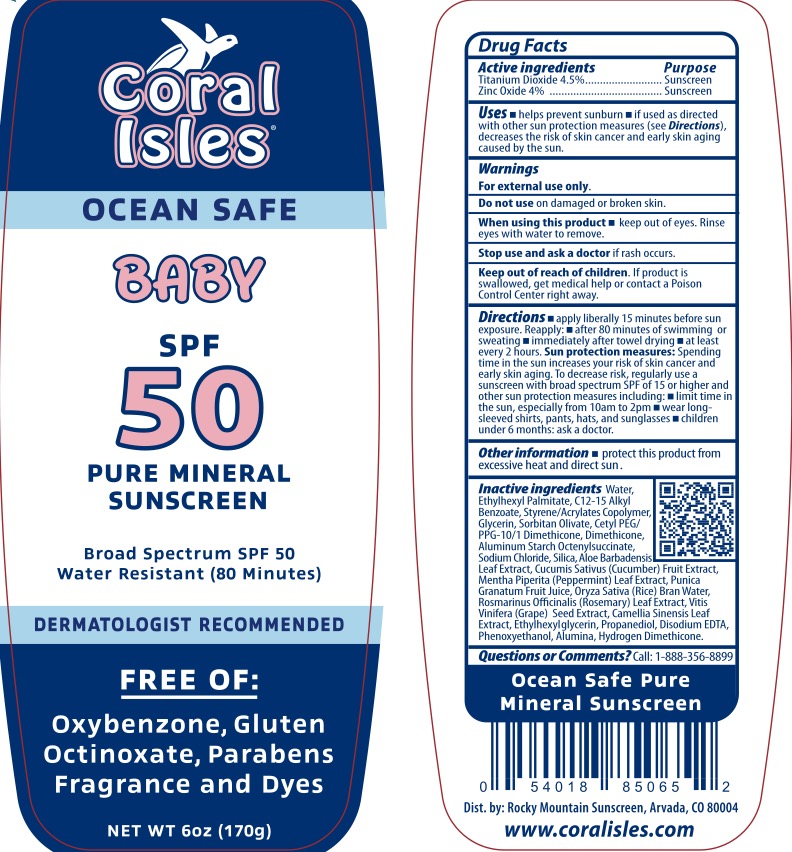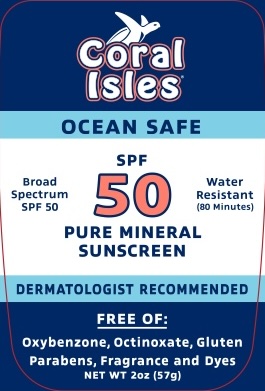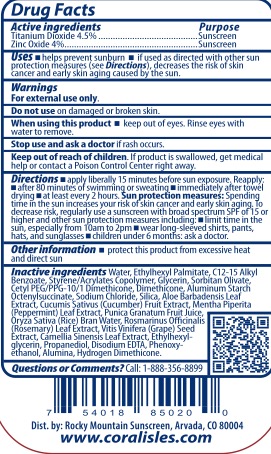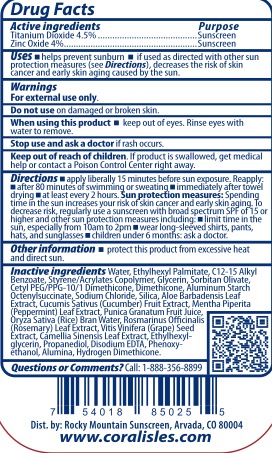 DRUG LABEL: Coral Isle SPF 50 Mineral Sunscreen
NDC: 72839-114 | Form: LOTION
Manufacturer: Derma Care Research Labs, LLC
Category: otc | Type: HUMAN OTC DRUG LABEL
Date: 20240102

ACTIVE INGREDIENTS: TITANIUM DIOXIDE 4.5 g/100 g; ZINC OXIDE 4 g/100 g
INACTIVE INGREDIENTS: ETHYLHEXYL PALMITATE; EDETATE DISODIUM; ALKYL (C12-15) BENZOATE; ALUMINUM STARCH OCTENYLSUCCINATE; STYRENE/ACRYLAMIDE COPOLYMER (MW 500000); GLYCERIN; ETHYLHEXYLGLYCERIN; PHENOXYETHANOL; CETYL PEG/PPG-10/1 DIMETHICONE (HLB 4); SORBITAN OLIVATE; DIMETHICONE 200; HYDRATED SILICA; WATER; HYDROGEN DIMETHICONE (20 CST); SODIUM CHLORIDE; ROSEMARY; VITIS VINIFERA SEED; GREEN TEA LEAF; ALUMINUM OXIDE; ALOE VERA LEAF; MENTHA PIPERITA LEAF; CUCUMBER; POMEGRANATE JUICE; RICE BRAN, DEFATTED; PROPANEDIOL

Coral Isle SPF 50 Mineral Lotion

Active Ingredients

Titanium Dioxide 4.4%, Zinc Oxide 4%

Purpose

Sunscreen

Uses

Helps prevent sunburn. If used as directed with other sun protection measures (see Directions), decreases the risk of skin cancer and early skin aging caused by the sun.

Warnings

For external use only.

Do not use on damaged or broken skin. When using this product keep out of eyes. Rinse eyes with water to remove.

Stop use and ask a doctor if rash occurs.

Keep Out of Reach of Children.

If swallowed, get medical help or contact a Poison Control Center right away.

Directions

Apply liberally 15 minutes before sun exposure. Reapply:

- after 80 minutes of swimming or sweating
- immediately after towel drying
- at least every 2 hours

Sun protection measures: spending time n the sun increases your risk of skin cancer and early skin aging. To decrease risk, regularly use a sunscreen with broad spectrum SPF of 15 or higher and other sun protection measure including:

- limit time in the sun, especially from 10 am to 2 pm
- wear long-sleeved shirts, pants, hats, and sunglasses.
- Children under 6 months: ask a doctor.

Inactive Ingredients

Water, ethylhexyl palmitate, C12-15 alkyl benzoate, styrene/acrylates copolymer, glycerin, sorbitan olivate, cetyl PEG/PPG-10/1 dimethicone, dimethicone, aluminum starch octenylsuccinate, sodium chloride, silica, aloe barbadensis leaf extract, cucumis sativus (cucumber) fruit extract, mentha piperita (peppermint) leaf extract, punica granatum fruit juice, oryza sativa (rice) bran water, rosmarinus officinalis (rosemary) leaf extract, vitis vinifera (grade) seed extract, camellia sinensis leaf extract, ethylhexylglycerin, propanediol, disodium EDTA, phenoxyethanol, alumina, hydrogen dimethicone

Label

Coral Isle SPF 50 Mineral Sunscreen, 2 oz, NDC 72839-114-02

Coral Isle Baby SPF 50 Mineral, 2 oz, NDC 72839-114-12

Coral Isle SPF 50 Mineral Sunscreen, 6 oz, NDC 72839-114-06

Coral Isle SPF 50 Baby Mineral Sunscreen, 6 oz, NDC 72839-114-16